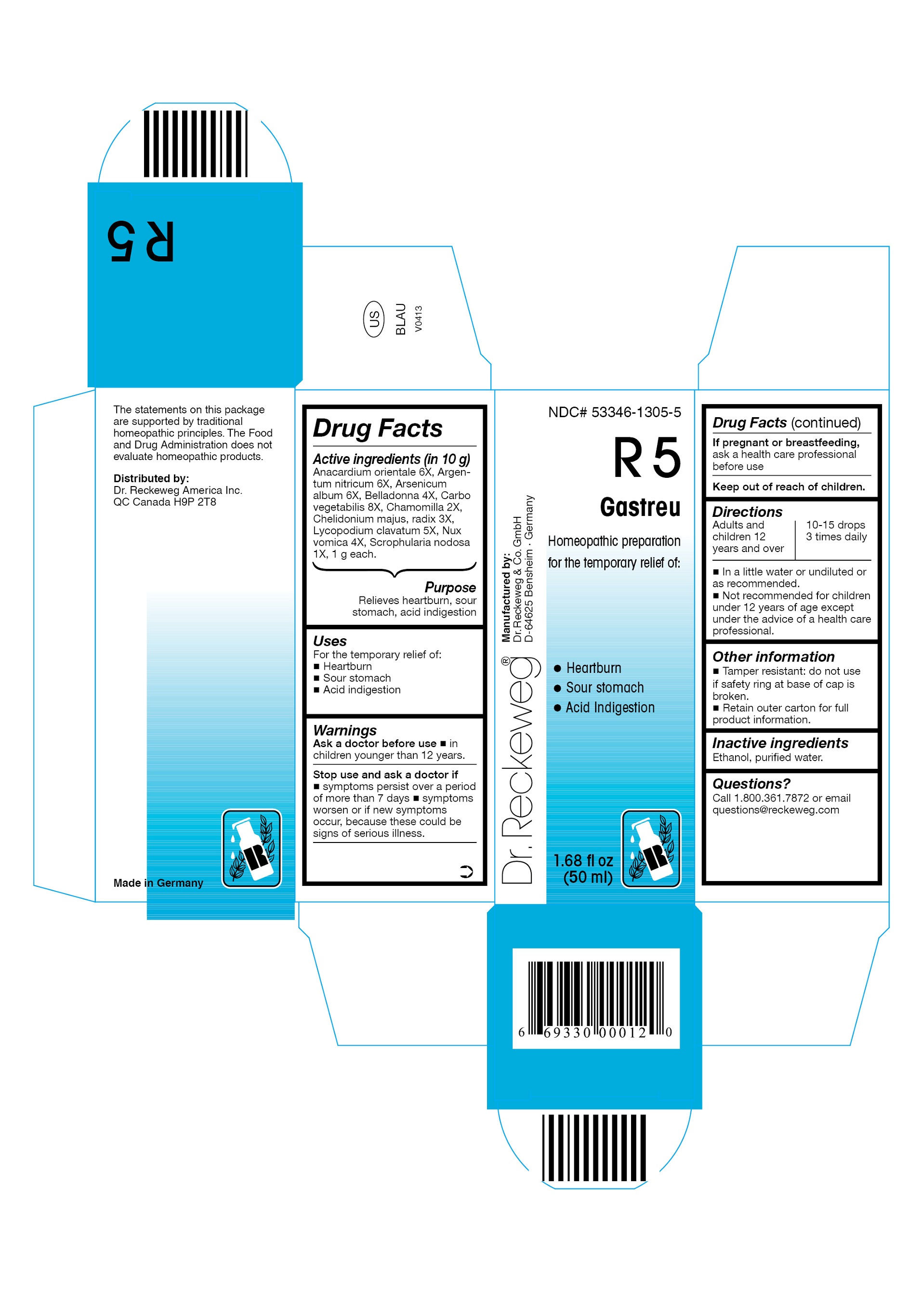 DRUG LABEL: Dr. RECKEWEG R5 Gastreu
NDC: 53346-1305 | Form: LIQUID
Manufacturer: PHARMAZEUTISCHE FABRIK DR. RECKEWEG & CO
Category: homeopathic | Type: HUMAN OTC DRUG LABEL
Date: 20130521

ACTIVE INGREDIENTS: SEMECARPUS ANACARDIUM FRUIT 6 [hp_X]/50 mL; SILVER NITRATE 6 [hp_X]/50 mL; ARSENIC TRIOXIDE 6 [hp_X]/50 mL; ATROPA BELLADONNA 4 [hp_X]/50 mL; ACTIVATED CHARCOAL 8 [hp_X]/50 mL; MATRICARIA RECUTITA 2 [hp_X]/50 mL; CHELIDONIUM MAJUS ROOT 3 [hp_X]/50 mL; LYCOPODIUM CLAVATUM SPORE 5 [hp_X]/50 mL; STRYCHNOS NUX-VOMICA SEED 4 [hp_X]/50 mL; SCROPHULARIA NODOSA 1 [hp_X]/50 mL
INACTIVE INGREDIENTS: ALCOHOL; WATER

Dr. RECKEWEG R5 Gastreu

Active ingredients:

Anacardium orientale 6X, Argentum nitricum 6X, Arsenicum album 6X, Belladonna 4X, Carbo vegetabilis 8X, Chamomilla 2X, Chelidonium majus, radix 3X, Lycopodium clavatum 5X, Nux vomica 4X, Scrophularia nodosa 1X, 1 g each in 10 g.

Purpose

Relieves heartburn, sour stomach, acid indigestion

Uses

For the temporary relief of:

- Heartburn
- Sour stomach
- Acid indigestion

Warnings

Ask a doctor before use

- in children younger than 12 years.

Stop use and ask a doctor if

- symptoms persist over a period of more than 7 days
- symptoms worsen or if new symptoms occur, because these could be signs of serious illness.

PREGNANCY OR BREAST FEEDING

If pregnant or breastfeeding, ask a health care professional before use.

Keep out of reach of children.

Directions
Adults and children ≥ 12 years 10-15 drops 3 times daily in a little water or undiluted or as recommended.

Not recommended for children under 12 years of age except under the advice of a health care professional.

Other information

- Tamper resistant: do not use if safety ring at base of cap is broken.
- Retain outer carton for full product information.

Inactive ingredients

Ethanol, purified water.

Questions?

Call 1-800-361-7872 or email questions@reckeweg.com

PACKAGE LABEL

NDC# 53346-1305-5

Dr. Reckeweg R5 Gastreu

Homeopathic preparation for the temporary relief of:

- Heartburn
- Sour stomach
- Acid indigestion

Manufactured by:

Dr. Reckeweg Co. GmbH

D-64625 Bensheim

Germany

1.68 fl oz
(50 ml)